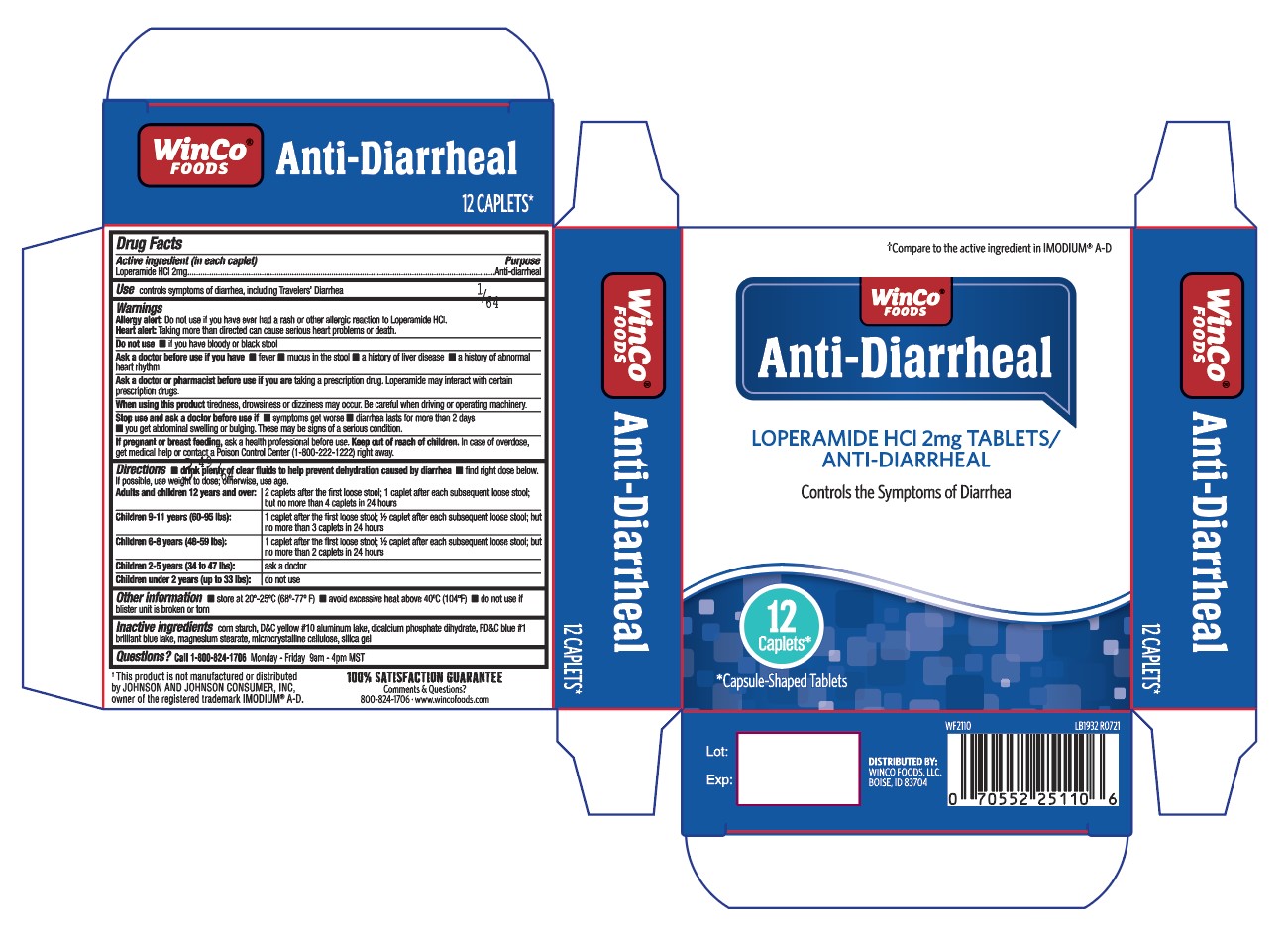 DRUG LABEL: Anti Diarrheal
NDC: 67091-405 | Form: CAPSULE
Manufacturer: WinCo Foods
Category: otc | Type: HUMAN OTC DRUG LABEL
Date: 20220106

ACTIVE INGREDIENTS: LOPERAMIDE HYDROCHLORIDE 2 mg/1 1
INACTIVE INGREDIENTS: STARCH, CORN; D&C YELLOW NO. 10 ALUMINUM LAKE; DIBASIC CALCIUM PHOSPHATE DIHYDRATE; MAGNESIUM STEARATE; FD&C BLUE NO. 1 ALUMINUM LAKE; MICROCRYSTALLINE CELLULOSE; SILICON DIOXIDE

248 - Anti Diarrheal

Active ingredient(s)

Loperamide HCl 2mg

Purpose

Anti-diarrheal

Use(s)

controls symptoms of diarrhea, including Travelers’ Diarrhea

Warnings

Allergy alert: Do not use if you have ever had a rash or other allergic reactions to loperamide HCl.

Heart alert: Taking more than directed can cause serious heart problems or death.

Do not use

- if you have bloody or black stool

Ask a doctor before use if

- fever
- mucus in the stool
- a history of liver disease
- a history of abnormal heart rhythm

Ask a doctor or pharmacist before use if

taking a prescription drug. Loperamide may interact with certain prescription drugs.

When using this product

tiredness, drowsiness, or dizziness may occur. Be careful when driving or operating machinery.

Stop use and ask a doctor if

- symptoms get worse
- diarrhea lasts for more than 2 days
- you get abdominal swelling or bulging.

These may be signs of a serious condition.

Pregnancy/Breastfeeding

ask a health professional before use.

Keep out of reach of children

In case of overdose, get medical help or contact a Poison Control Center (1-800-222-1222) right away.

Directions

- drink plenty of clear fluids to help prevent dehydration caused by diarrhea
- find right dose below. If possible, use weight to dose; otherwise, use age.
- adults and children 12 years and over: 2 caplets after the first loose stool; 1 caplet after each subsequent loose stool; but no more than 4 caplets in 24 hours
- children 9-11 years (60-95 lbs): 1 caplet after the first loose stool; ½ caplet after each subsequent loose stool; but no more than 3 caplets in 24 hours
- children 6-8 years (48-59 lbs): 1 caplet after the first loose stool; ½ caplet after each subsequent loose stool; but no more than 2 caplets in 24 hours
- children 2-5 years (34 to 47 lbs): ask a doctor
- children under 2 years (up to 33 lbs): do not use

Other information

store at 20º-25ºC (68º-77º F)

avoid excessive heat above 40ºC (104ºF)

do not use if blister unit is broken or torn

Inactive ingredients

corn starch, D&C yellow #10
aluminum lake, dicalcium phosphate dihydrate, FD&C
blue #1 brilliant blue lake, magnesium stearate,
microcrystalline cellulose, silica gel

Questions

Call 1-800-824-1706 Monday - Friday 9AM - 4PM MST

Principal Display Panel

Anti Diarrheal